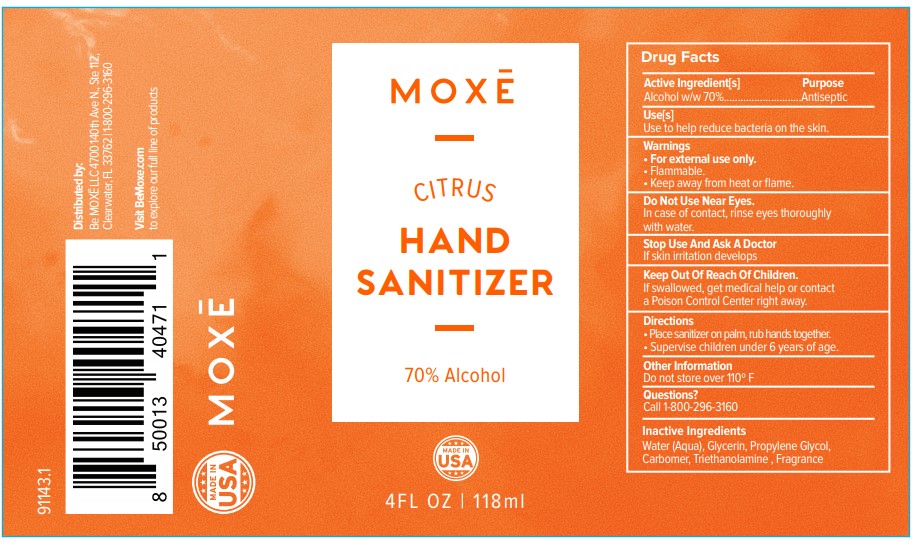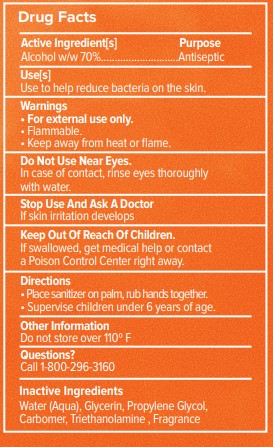 DRUG LABEL: Moxe
NDC: 73333-011 | Form: GEL
Manufacturer: Nutrix International, LLC.
Category: otc | Type: HUMAN OTC DRUG LABEL
Date: 20200511

ACTIVE INGREDIENTS: ALCOHOL 0.7 g/118 g
INACTIVE INGREDIENTS: TANGERINE 0.005 g/118 g; TROLAMINE 0.0012 g/118 g; CARBOMER 940 0.004 g/118 g; PROPYLENE GLYCOL 0.015 g/118 g; WATER 0.2598 g/118 g; GLYCERIN 0.015 g/118 g

Active Ingredient[s]

Alcohol 70%

Use[s]

Use to help reduce bacteria on the skin.

Warnings

• For external use only.

• Flammable.

• Keep away from heat or flame.

Do Not Use Near Eyes. In case of contact, rinse eyes thoroughly with water.

Stop Use And Ask

A Doctor If skin irritation develops

Keep out of reach of children

If swallowed, get medical help or contacta Poison Control Center right away

Directions

• Place sanitizer on palm, rub hands together.

• Supervise children under 6 years of age.

Other Information

Do not store over 110º F

Inactive Ingredients

Water (Aqua), Glycerin, Propylene Glycol, Carbomer, Triethanolamine, Fragrance

Purpose

Antiseptic

Artwork

Label